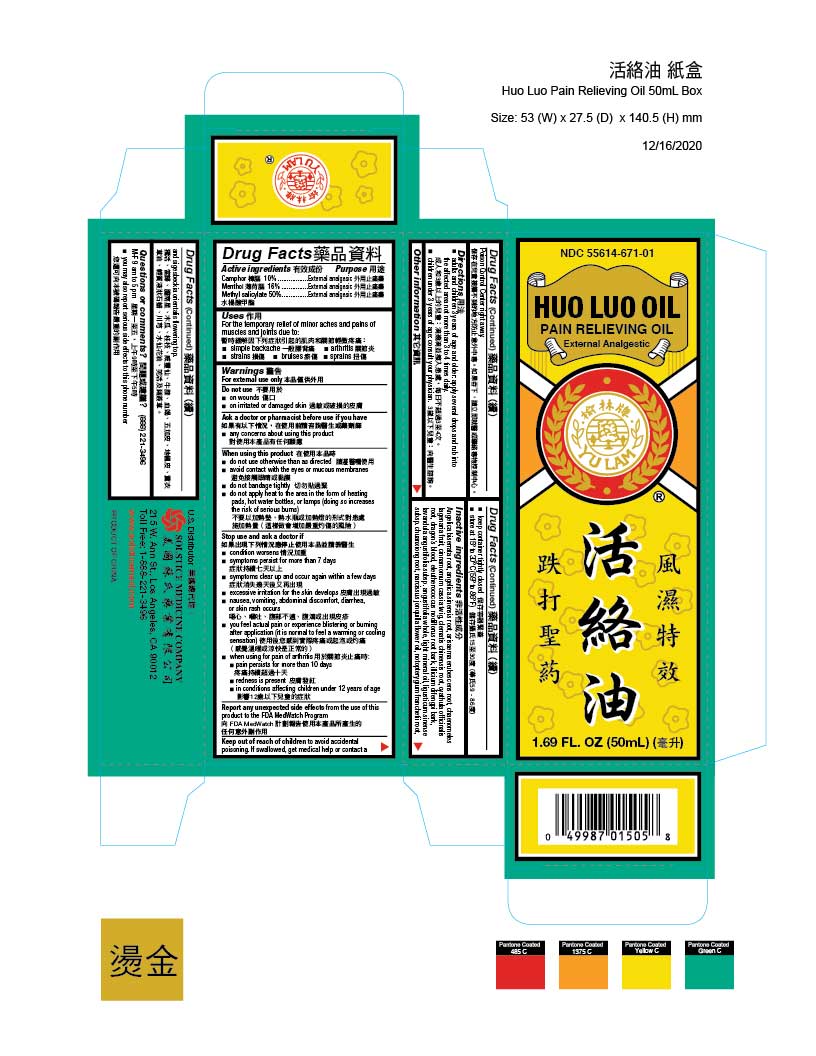 DRUG LABEL: HUO LUO PAIN RELIEVING
NDC: 55614-671 | Form: OIL
Manufacturer: MADISON ONE ACME INC
Category: otc | Type: HUMAN OTC DRUG LABEL
Date: 20251110

ACTIVE INGREDIENTS: CAMPHOR (SYNTHETIC) 10 g/100 mL; MENTHOL 16 g/100 mL; METHYL SALICYLATE 50 g/100 mL
INACTIVE INGREDIENTS: ANGELICA BISERRATA ROOT; ANGELICA SINENSIS ROOT; ARISAEMA ERUBESCENS ROOT; CHAENOMELES LAGENARIA FRUIT; CINNAMOMUM CASSIA TWIG; CLEMATIS CHINENSIS ROOT; CYATHULA OFFICINALIS ROOT; DRAGON'S BLOOD; ELEUTHEROCOCCUS NODIFLORUS ROOT BARK; ILLICIUM DIFENGPI BARK; LAVANDULA ANGUSTIFOLIA SUBSP. ANGUSTIFOLIA WHOLE; LIGHT MINERAL OIL; LIGUSTICUM SINENSE SUBSP. CHUANXIONG ROOT; NARCISSUS JONQUILLA FLOWER OIL; INCISED NOTOPTERYGIUM RHIZOME OR ROOT (NOTOPTERYGIUM FRANCHETII); SIGESBECKIA ORIENTALIS FLOWERING TOP

Drug Facts

Active ingredients
Camphor 10%
Menthol 16%
Methyl salicylate 50%

Purpose
External analgesic
External analgesic
External analgesic

Uses
For the temporary relief of minor aches and pains of muscles and joints due to:
■ simple backache
■ arthritis
■ strains
■ bruises
■ sprains

Warnings
For external use only

Do not use
■ on wounds
■ on irritated or damaged skin

Ask a doctor or pharmacist before use if you have
■ any concerns about using this product

When using this product
■ do not use otherwise than as directed
■ avoid contact with the eyes or mucous membranes
■ do not bandage tightly
■ do not apply heat to the area in the form of heating pads, hot water bottles, or lamps (doing so increases the risk of serious burns)

Stop use and ask a doctor if
■ condition worsens
■ symptoms persist for more than 7 days
■ symptoms clear up and occur again within a few days
■ excessive irritation of the skin develops
■ nausea, vomiting, abdominal discomfort, diarrhea, or skin rash occurs
■ you feel actual pain or experience blistering or burning after application (it is normal to feel a warming or cooling sensation)
■ when using for pain of arthritis:
■ pain persists for more than 10 days
■ redness is present
■ in conditions affecting children under 12 years of age

ADVERSE REACTIONS

Report any unexpected side effectsfrom the use of this product to the FDA MedWatch Program

KEEP OUT OF REACH OF CHILDREN

Keep out of reach of childrento avoid accidental poisoning. If swallowed, get medical help or contact a Poison Control Center right away.

Directions
■ adults and children 3 years of age and older: apply several drops and rub Into the affected area not more than 3 to 4 times daily
■ children under 3 years of age: consult your physician

Other information
■ keep container tightly closed
■ store protected from light at 15 to 30 C (59 to 86 F)

Inactive ingredients
Angelica biserrata root, angelica sinensis root, arisaema erubescens root, chaenomeles lagenaria fruit, cinnamomum cassia twig, clematis chinensis root, cyathula officinalis root, dragon’s blood, eleutherococcus nodiflorus root bark, illicium difengpi bark, lavandula angustifolia subsp. angustifolia whole, light mineral oil, ligusticum sinense subsp. chuanxiong root, narcissus jonquilla flower oil, notopterygium franchetii root, and sigesbeckia orientalis flowering top.

Questions or comments? (888) 221-3496M-F 9 am to 5 pm
■ you may also report serious side effects to this phone number

PACKAGE LABEL

HUO LUO PAIN RELIEVING OIL

NDC 55614-671-01

EXTERNAL ANALGESIC

1.69 FL OZ (50 ML)